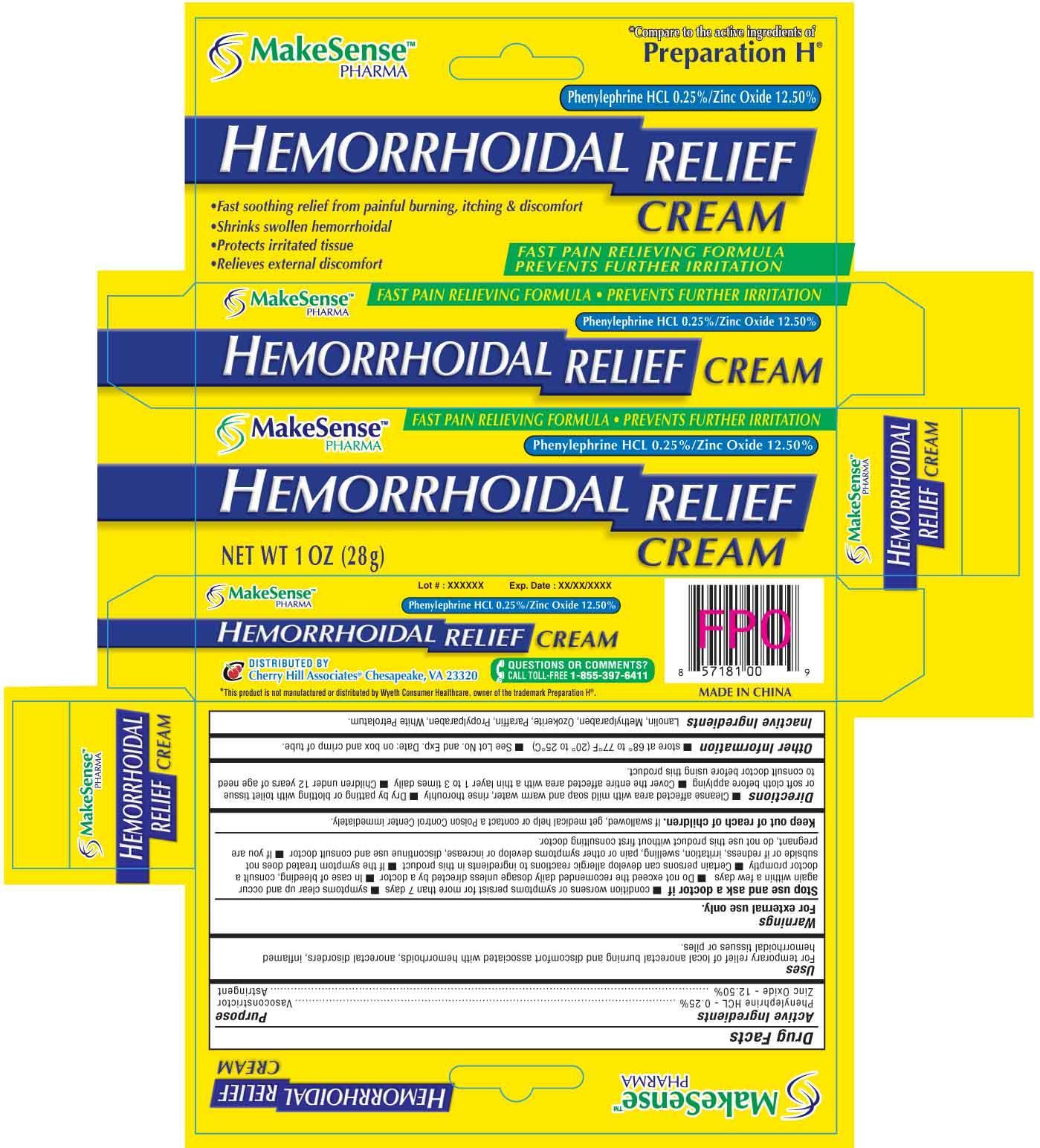 DRUG LABEL: MAKESENSE
NDC: 69020-205 | Form: CREAM
Manufacturer: Cherry Hill Sales Co
Category: otc | Type: HUMAN OTC DRUG LABEL
Date: 20140811

ACTIVE INGREDIENTS: PHENYLEPHRINE HYDROCHLORIDE 0.25 g/100 g; ZINC OXIDE 12.5 g/100 g
INACTIVE INGREDIENTS: CERESIN; LANOLIN; METHYLPARABEN; PARAFFIN; PETROLATUM; PROPYLPARABEN

Drug Facts

Active Ingredient

Phenylephrine HCL 0.25%

Zinc Oxide 12.50%

Purpose

Vasoconstrictor

Astringent

Uses

For temporary relief of local anorectal burning and discomfort associated with hemorrhoids, anorectal disorders, inflamed hemorrhoidal tissues or piles.

Warnings

For external use only

Do not use

■ on children under 2 years of age except under the advise and supervision of a doctor ■ for diaper rash

Stop use and ask a doctor if

■ condition worsens or symptoms persist for more than 7 days ■ symptoms clear up and occur again within a few days ■ Do not exceed the recomended daily dosage unless directed by a doctor ■ In case of bleeding, consult a doctor promptly ■ Certain persons can develop allergic reactions to ingredients in this product ■ If the symptom treated does not subside or if redness, irritation, swelling, pain or other symptoms develop or increase, discontinue use and consult doctor ■ If you are pregnant, do not use this product without first consulting doctor.

Keep out of reach of children

If swallowed, get medical help or contact a Poison Control Center right away

Directions

■ Cleanse affected area with mild soap and warm water, rinse thorouhly ■ Dry by patting or blotting with toilet tissue
or soft cloth before applying ■ Cover the entire affected area with a thin layer 1 to 3 times daily ■ Children under 12 years of age need
to consult doctor before using this product

Other information

■ store at 68-77F (20 to 25C) ■ See Lot No. and Exp. Date: on box and crimp of tube

Inactive Ingredients

Lanolin, Methylparaben, Ozokerite, Paraffin, Propylparaben, White Petrolatum